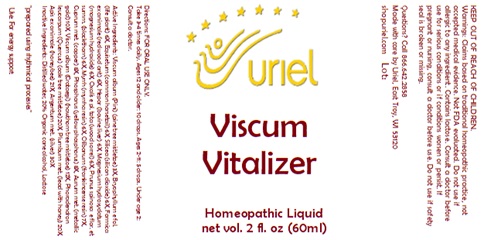 DRUG LABEL: Viscum Vitalizer
NDC: 48951-9375 | Form: LIQUID
Manufacturer: Uriel Pharmacy, Inc.
Category: homeopathic | Type: HUMAN OTC DRUG LABEL
Date: 20240906

ACTIVE INGREDIENTS: FRANKINCENSE 7 [hp_X]/1 mL; COPPER 8 [hp_X]/1 mL; HAWTHORN LEAF WITH FLOWER 12 [hp_X]/1 mL; VISCUM ALBUM FRUITING TOP 3 [hp_X]/1 mL; APIS MELLIFERA 21 [hp_X]/1 mL; MYRRH 7 [hp_X]/1 mL; PHOSPHORUS 8 [hp_X]/1 mL; LEAD 20 [hp_X]/1 mL; BEEF LIVER 6 [hp_X]/1 mL; SILVER 30 [hp_X]/1 mL; EQUISETUM ARVENSE TOP 6 [hp_X]/1 mL; MAGNESIUM HYDROXIDE 6 [hp_X]/1 mL; PHORADENDRON LEUCARPUM FRUITING TOP 20 [hp_X]/1 mL; SLOE 6 [hp_X]/1 mL; GOLD 10 [hp_X]/1 mL; KALANCHOE DAIGREMONTIANA LEAF 6 [hp_X]/1 mL; FORMICA RUFA 6 [hp_X]/1 mL; SILICON DIOXIDE 6 [hp_X]/1 mL; OXALIS STRICTA WHOLE 6 [hp_X]/1 mL
INACTIVE INGREDIENTS: LACTOSE, UNSPECIFIED FORM; WATER; ALCOHOL

Viscum Vitalizer

INDICATIONS AND USAGE

Directions: FOR ORAL USE ONLY.

DOSAGE AND ADMINISTRATION

Take 3-4 times daily. Ages 12 and older: 10 drops. Ages 2-11: 5 drops. Under age 2: Consult a doctor.

ACTIVE INGREDIENT

Active Ingredients: Viscum album (Pini) (pine tree mistletoe) 3X, Bryophyllum e fol. (life plant) 6X, Equisetum (common horsetail) 6X, Silicea (silicon dioxide) 6X, Formica ex animale (red wood ant) 6X, Hepar (bovine liver) 6X, Magnesium hydroxydatum (magnesium hydroxide) 6X, Oxalis e pl. tota (wood sorrel) 6X, Prunus spinosa e flor. et summ. (blackthorn) 6X, Myrrh (myrrha resin) 6X, Olibanum (frankincense resin) 7X, Cuprum met. (copper) 8X, Phosphorus (yellow phosphorus) 8X, Aurum met. (metallic gold) 10X, Viscum album (Crataegi) (hawthorn tree mistletoe) 12X, Phoradendron leucarpum (Quercus) (oak tree mistletoe) 20X, Plumbum met. (lead with honey) 20X, Apis ex animale (honeybee) 21X, Argentum met. (silver) 30X

INACTIVE INGREDIENT

Inactive Ingredients: Distilled water, 20% Organic cane alcohol, Lactose

Prepared using rhythmical processes

PURPOSE

Use: For energy support

KEEP OUT OF REACH OF CHILDREN.

WARNINGS

Warnings: Claims based on traditional homeopathic practice, not accepted medical evidence. Not FDA evaluated. Do not use if allergic to any ingredient. Contains traces of lactose. Consult a doctor before use for serious conditions or if conditions worsen or persist. If pregnant or nursing, consult a doctor before use. Do not use if safety seal is broken or missing.

Questions? Call 866.642.2858
Made with care by Uriel, East Troy, WI 53120
shopuriel.com Lot: